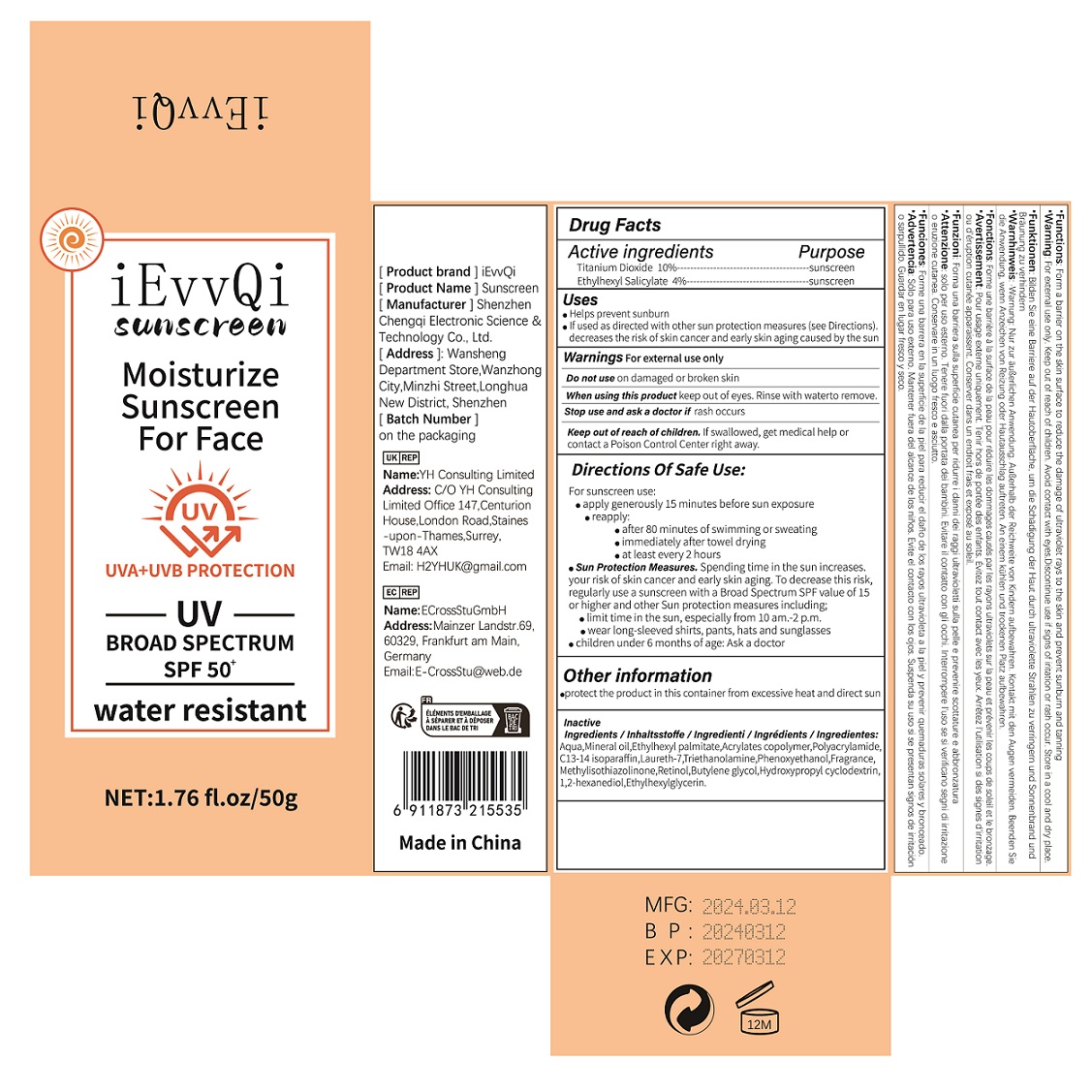 DRUG LABEL: Sunscreen
NDC: 84118-002 | Form: LOTION
Manufacturer: Shenzhen Chengqi Electronic Science & Technology Co., Ltd.
Category: otc | Type: HUMAN OTC DRUG LABEL
Date: 20240309

ACTIVE INGREDIENTS: TITANIUM DIOXIDE 100 mg/1 g
INACTIVE INGREDIENTS: WATER

ACTIVE INGREDIENT :

Titanium Dioxide 10%

Ethylhexyl salicylate 4%

INACTIVE INGREDIENT

AQUA

MINERAL OIL

ETHYLHEXYL PALMITATE

ACRYLATES COPOLYMER

POLYACRYLAMIDE

C13-14 ISOPARAFFIN

LAURETH-7

TRIETHANOLAMINE

PHENOXYETHANOL

FRAGRANCE

METHYLISOTHIAZOLINONE

RETINOL

BUTYLENE GLYCOL

HYDROXYPROPYL CYCLODEXTRIN

1,2-HEXANEDIOL

ETHYLHEXYLGLYCERIN

Purpose

sunscreen

Uses

Helps prevent sunburn
If used as directed with other sun protection measures (see Directions). decreases the risk of skin cancer and early skin aging caused by the sun

WARNINGS

For external use only

Stop use and ask a doctor if

rash occurs

DO NOT USE

on damaged or broken skin

When using this product

keep out of eyes. Rinse with water to remove

Keep out of reach of children.

If swallwed, get medical help or contact a Poison Control Center right away

DOSAGE & ADMINISTRATION

Take an appropriate amount of this product and apply it to the skin